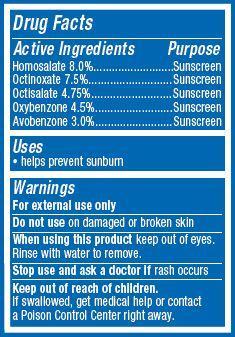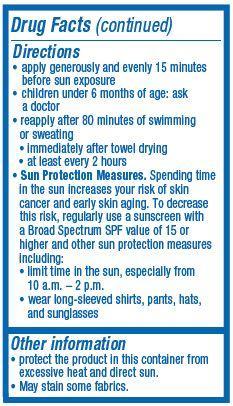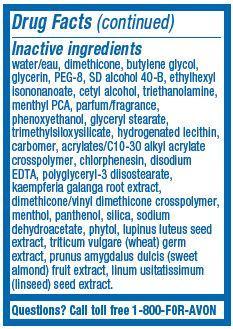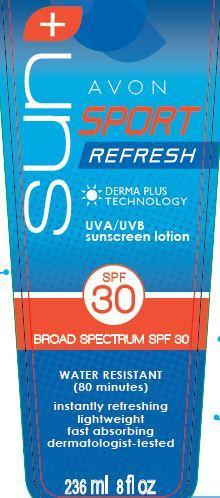 DRUG LABEL: Avon Sun Sport
NDC: 10096-0314 | Form: LOTION
Manufacturer: New Avon LLC
Category: otc | Type: HUMAN OTC DRUG LABEL
Date: 20160219

ACTIVE INGREDIENTS: HOMOSALATE 80 mg/1 mL; OCTINOXATE 75 mg/1 mL; OCTISALATE 47.5 mg/1 mL; OXYBENZONE 45 mg/1 mL; AVOBENZONE 30 mg/1 mL

Active ingredients

Homosalate 8.0%...................
Octinoxate 7.5%....................
Octisalate 4.75%...................
Oxybenzone 4.5%...............
Avobenzone 3.0%................

Purpose
.................................Sunscreen

.................................Sunscreen

.................................Sunscreen

.................................Sunscreen

.................................Sunscreen

Uses
• helps prevent sunburn

Warnings
For external use only

Do not use on damaged or broken skin

When using this product

- keep out of eyes. Rinse with water to remove.

Stop use and ask a doctor if rash occurs

Keep out of reach of children.

If swallowed, get medical help or contact a Poison Control Center right away.

Directions
• apply generously and evenly 15 minutes before sun exposure
• children under 6 months of age: ask a doctor
• reapply after 80 minutes of swimming or sweating
• immediately after towel drying

• at least every 2 hours

• Sun Protection Measures. Spending time in the sun increases your risk of skin cancer and early skin aging. To decrease this risk, regularly use a sunscreen with a Broad Spectrum SPF value of 15 or higher and other sun protection measures including:
• limit time in the sun, especially from 10 a.m. – 2 p.m.
• wear long-sleeved shirts, pants, hats, and sunglasses

Other information

• protect the product in this container from excessive heat and direct sun

• May stain some fabrics.

Inactive Ingredients:
water/eau, dimethicone, butylene glycol, glycerin, PEG-8, SD alcohol 40-B, ethylhexyl isononanoate, cetyl alcohol, triethanolamine, menthyl PCA, parfum/fragrance, phenoxyethanol, glyceryl stearate, trimethylsiloxysilicate, hydrogenated lecithin, carbomer, acrylates/C10-30 alkyl acrylate crosspolymer, chlorphenesin, disodium EDTA, polyglyceryl-3 diisostearate, kaempferia galanga root extract, dimethicone/vinyl dimethicone crosspolymer, menthol, panthenol, silica, sodium dehydroacetate, phytol, lupinus luteus seed extract, triticum vulgare (wheat) germ extract, prunus amygdalus dulcis (sweet almond) fruit extract, linum usitatissimum (linseed) seed extract.

Questions?
Call toll free 1-800-FOR-AVON